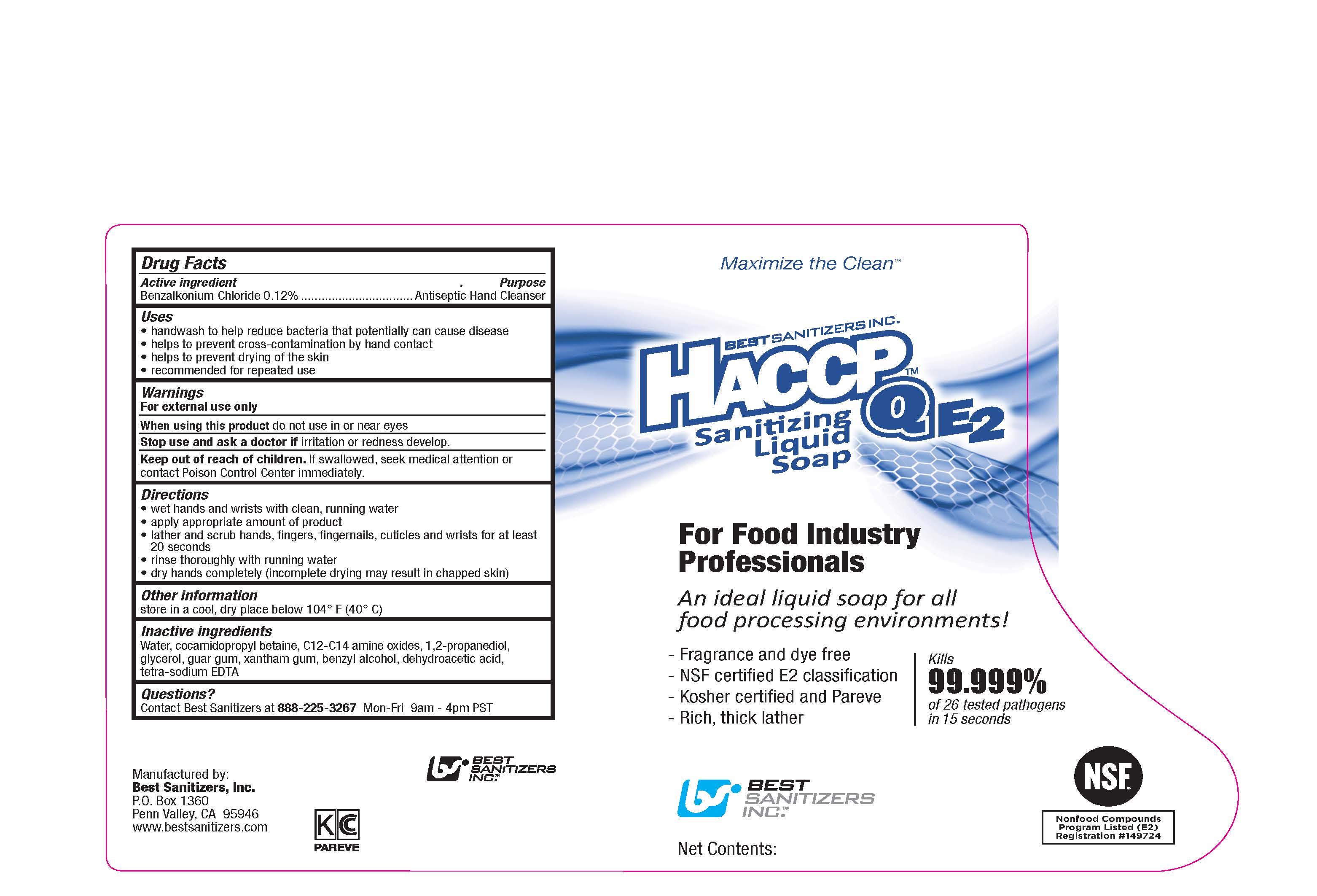 DRUG LABEL: HACCP Q E2 Sanitizing
NDC: 59900-215 | Form: LIQUID
Manufacturer: Best Sanitizers, Inc.
Category: otc | Type: HUMAN OTC DRUG LABEL
Date: 20241205

ACTIVE INGREDIENTS: BENZALKONIUM CHLORIDE 1.2 mg/1 mL
INACTIVE INGREDIENTS: WATER; COCAMIDOPROPYL BETAINE; LAURAMINE OXIDE; PROPYLENE GLYCOL; GLYCERIN; GUAR GUM; XANTHAN GUM; BENZYL ALCOHOL; DEHYDROACETIC ACID; EDETATE SODIUM

Drug Facts 59900-215

Active ingredient

Benzalkonium Chloride 0.12%

Purpose

Antiseptic Hand Cleanser

Uses

- handwash to help reduce bacteria that potentially can cause disease

- helps to prevent cross-contamination by hand contact

- helps to prevent drying of the skin

- recommended for repeated use

Warnings

For external use only

WHEN USING

When using this productdo not use in or near eyes

Stop use and ask a doctor ifirritation or redness develop.

Keep out of reach of children.

If swallowed, seek medical attention or contact Poison Control Center immediately.

Directions

- wet hands and wrists with clean, running water

- apply appropriate amount of product

- lather and scrub hands, fingers, fingernails, cuticles and wrists for at least 20 seconds

- rinse thoroughly with running water

- dry hands completely (incomplete drying may result in chapped skin)

Other information

store in a cool, dry place below 104oF (40oC)

Inactive ingredients

Water, cocamipopropyl betaine, C12-C14 amine oxides, 1,2-propanediol, glycerol, guar gum, xatham gum, benzyl alcohol, dehydroacetic acid, tetra-sodium EDTA

Questions?

Contact Best Sanitizers at 888-225-3267Mon-Fri 9am - 4 pm PST

PACKAGE LABEL

Maximize the Clean

BEST SANITIZERS INC.

HACCP Q E2

Sanitizing

Liquid

Soap

For Food Industry

Professionals

An ideal liquid soap for all food processing environments!

Fragrance and dye free

NSF certified E2 classification

Kosher certified and Pareve

Rich, thick lather

Kills

99.999%

of 26 tested pathogens

in 15 seconds

BEST SANITIZERS INC.

NSF

Nonfood Compounds

Program Listed (E2)

Registration Number 149724

Net Contents: